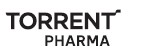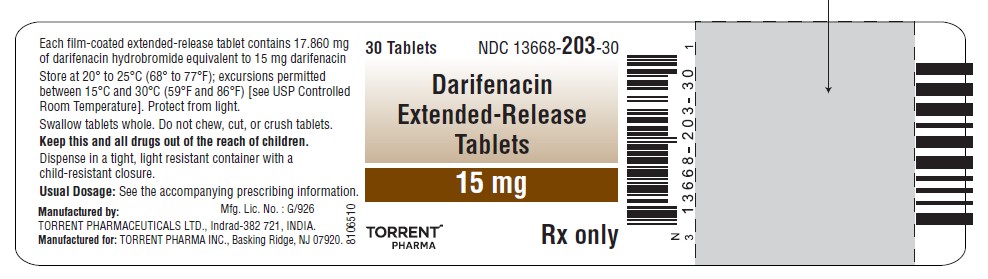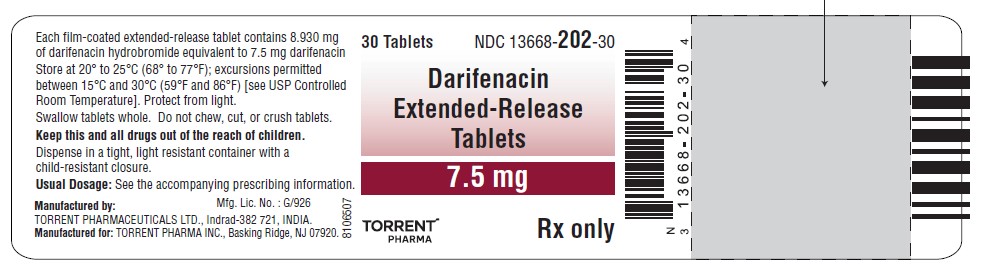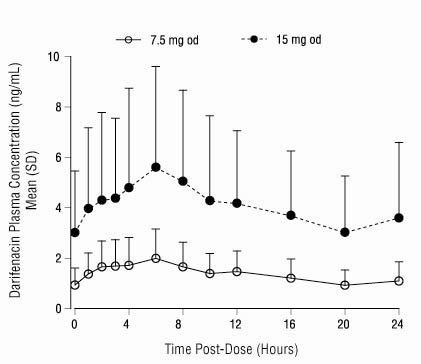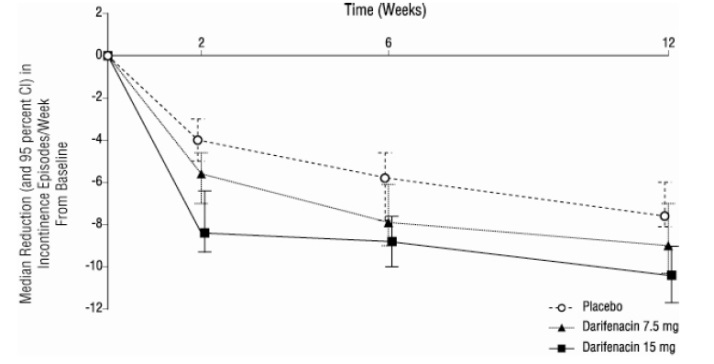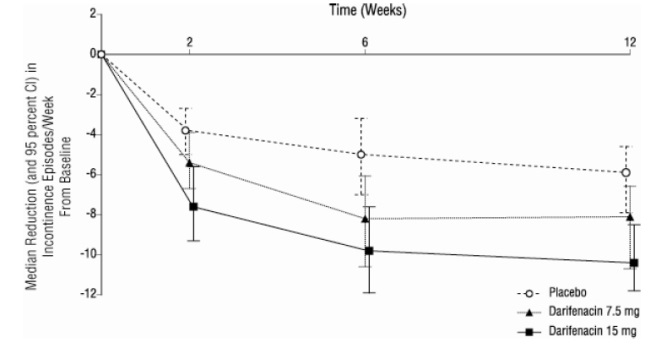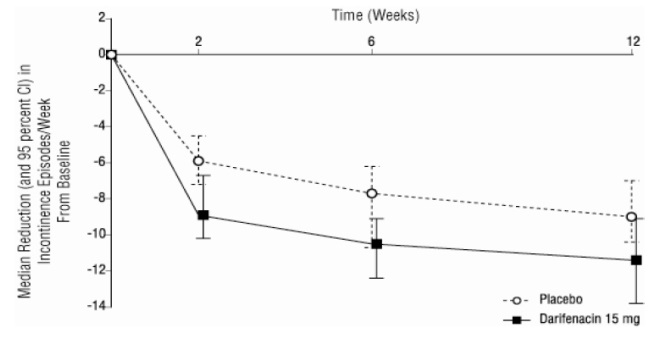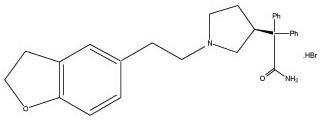 DRUG LABEL: Darifenacin
NDC: 13668-202 | Form: TABLET, EXTENDED RELEASE
Manufacturer: Torrent Pharmaceuticals Limited
Category: prescription | Type: HUMAN PRESCRIPTION DRUG LABEL
Date: 20260210

ACTIVE INGREDIENTS: DARIFENACIN HYDROBROMIDE 7.5 mg/1 1
INACTIVE INGREDIENTS: CELLULOSE, MICROCRYSTALLINE; HYPROMELLOSE 2208 (4000 MPA.S); HYPROMELLOSE 2910 (15 MPA.S); MAGNESIUM STEARATE; POLYETHYLENE GLYCOL 400; SILICON DIOXIDE; TALC; TITANIUM DIOXIDE

HIGHLIGHTS OF PRESCRIBING INFORMATION

These highlights do not include all the information needed to use DARIFENACIN EXTENDED-RELEASE TABLETS safely and effectively. See full prescribing information for DARIFENACIN EXTENDED-RELEASE TABLETS.
DARIFENACIN extended-release tablets, for oral use
Initial U.S. Approval:2004

1 INDICATIONS AND USAGE

Darifenacin extended-release tablets are a muscarinic antagonist indicated for the treatment of overactive bladder with symptoms of urge urinary incontinence, urgency and frequency. (1)

2 DOSAGE AND ADMINISTRATION

The recommended starting dose of darifenacin extended-release tablets is 7.5 mg once daily. Based upon individual response, the dose may be increased to 15 mg once daily, as early as two weeks after starting therapy (2)

The daily dose of darifenacin extended-release tablets should not exceed 7.5 mg in the following patients:

- Patients with moderate hepatic impairment (Child-Pugh B) (2, 8.6)
- Patients taking potent CYP3A4 inhibitors (2, 7.1)

Darifenacin extended-release tablets is not recommended for use in patients with severe hepatic impairment (Child-Pugh C) (2, 8.6)

Darifenacin extended-release tablets may be taken with or without food. The tablet should be swallowed whole with water and not chewed, divided or crushed (2)

3 DOSAGE FORMS AND STRENGTHS

Extended-release tablets 7.5 mg and 15 mg (3)

4 CONTRAINDICATIONS

Darifenacin extended-release tablets is contraindicated in patients with, or at risk for, the following conditions (4):

- urinary retention,
- gastric retention, or
- uncontrolled narrow-angle glaucoma.

5 WARNINGS AND PRECAUTIONS

- Darifenacin extended-release tablets should be administered with caution to patients with clinically significant bladder outflow obstruction because of the risk of urinary retention (5.1)
- Darifenacin extended-release tablets should be administered with caution to patients with gastrointestinal obstructive disorders because of the risk of gastric retention (5.2)
- Darifenacin extended-release tablets should be used with caution in patients being treated for narrow-angle glaucoma and only where the potential benefits outweigh the risks (5.3)
- Central Nervous System Effects: Somnolence has been reported with darifenacin. Advise patients not to drive or operate heavy machinery until they know how darifenacin affects them (5.5)

6 ADVERSE REACTIONS

The most frequently reported adverse reactions (greater than 3 %) for darifenacin extended-release tablets are: constipation, dry mouth, headache, dyspepsia, nausea, urinary tract infection, accidental injury, and flu symptoms (6)

To report SUSPECTED ADVERSE REACTIONS, contact TORRENT PHARMA INC. at 1-800-912-9561 or FDA at 1-800-FDA-1088 or www.fda.gov/medwatch

7 DRUG INTERACTIONS

- Caution should be taken when darifenacin extended-release tablets is used concomitantly with medications that are predominantly metabolized by CYP2D6 and which have a narrow therapeutic window, such as flecainide, thioridazine and tricyclic antidepressants (7.2)
- The concomitant use of darifenacin extended-release tablets with other anticholinergic agents may increase the frequency and/or severity of dry mouth, constipation, blurred vision and other anticholinergic pharmacological effects. Anticholinergic agents may potentially alter the absorption of some concomitantly administered drugs due to effects of gastrointestinal motility (7.3)

8 USE IN SPECIFIC POPULATIONS

- Pregnancy: Darifenacin extended-release tablets should be used during pregnancy only if the benefit to the mother outweighs the potential risk to the fetus (8.1)
- Nursing Mothers: It is not known whether darifenacin is excreted into human milk and therefore caution should be exercised before darifenacin extended-release tablets are administered to a nursing woman (8.3)
- Pediatric Use: The safety and effectiveness of darifenacin extended- release tablets in pediatric patients have not been established (8.4)

FULL PRESCRIBING INFORMATION

1 INDICATIONS AND USAGE

Darifenacin extended-release tablets are indicated for the treatment of overactive bladder with symptoms of urge urinary incontinence, urgency and frequency.

2 DOSAGE AND ADMINISTRATION

The recommended starting dose of darifenacin extended-release tablets is 7.5 mg orally once daily. Based upon individual response, the dose may be increased to 15 mg once daily, as early as two weeks after starting therapy.

Darifenacin extended-release tablets should be taken orally once daily with water. Darifenacin extended-release tablets may be taken with or without food, and should be swallowed whole and not chewed, divided or crushed.

For patients with moderate hepatic impairment (Child-Pugh B) or when co-administered with potent CYP3A4 inhibitors (for example, ketoconazole, itraconazole, ritonavir, nelfinavir, clarithromycin and nefazadone), the daily dose of darifenacin extended-release tablets should not exceed 7.5 mg. Darifenacin extended-release tablets are not recommended for use in patients with severe hepatic impairment (Child-Pugh C) [see Warnings & Precautions (5.6), Drug Interactions (7.1), Use in Specific Populations (8.6) and Clinical Pharmacology (12.3)] .

3 DOSAGE FORMS AND STRENGTHS

Darifenacin extended-release tablets 7.5 mg are white to off-white colored, round, biconvex, bevel edged, film coated tablets, debossed "202" on one side and plain on other side.

Darifenacin extended-release tablets 15 mg are light peach colored, round, biconvex, bevel edged, film coated tablets, debossed "203" on one side and plain on other side.

4 CONTRAINDICATIONS

Darifenacin extended-release tablets are contraindicated in patients with, or at risk for, the following conditions:

- urinary retention
- gastric retention, or
- uncontrolled narrow-angle glaucoma.

5 WARNINGS AND PRECAUTIONS

5.1 Risk of Urinary Retention

Darifenacin extended-release tablets should be administered with caution to patients with clinically significant bladder outflow obstruction because of the risk of urinary retention.

5.2 Decreased Gastrointestinal Motility

Darifenacin extended-release tablets should be administered with caution to patients with gastrointestinal obstructive disorders because of the risk of gastric retention. Darifenacin extended-release tablets, like other anticholinergic drugs, may decrease gastrointestinal motility and should be used with caution in patients with conditions such as severe constipation, ulcerative colitis, and myasthenia gravis.

5.3 Controlled Narrow-Angle Glaucoma

Darifenacin extended-release tablets should be used with caution in patients being treated for narrow-angle glaucoma and only where the potential benefits outweigh the risks.

5.4 Angioedema

Angioedema of the face, lips, tongue, and/or larynx have been reported with darifenacin. In some cases angioedema occurred after the first dose. Angioedema associated with upper airway swelling may be life threatening. If involvement of the tongue, hypopharynx, or larynx occurs, darifenacin should be promptly discontinued and appropriate therapy and/or measures necessary to ensure a patent airway should be promptly provided.

5.5 Central Nervous System Effects

Darifenacin extended-release tablets are associated with anticholinergic central nervous system (CNS) effects [see Adverse Reactions (6.2)] . A variety of CNS anticholinergic effects have been reported, including headache, confusion, hallucinations and somnolence. Patients should be monitored for signs of anticholinergic CNS effects, particularly after beginning treatment or increasing the dose. Advise patients not to drive or operate heavy machinery until they know how darifenacin extended-release tablets affect them. If a patient experiences anticholinergic CNS effects, dose reduction or drug discontinuation should be considered.

5.6 Patients with Hepatic Impairment

The daily dose of darifenacin extended-release tablets should not exceed 7.5 mg for patients with moderate hepatic impairment (Child-Pugh B). Darifenacin extended-release tablets have not been studied in patients with severe hepatic impairment (Child-Pugh C) and therefore is not recommended for use in this patient population [see Dosage and Administration (2) Use in Specific Populations (8.6) and Clinical Pharmacology (12.3)] .

6 ADVERSE REACTIONS

6.1 Clinical Trials Experience

Because clinical trials are conducted under widely varying conditions, adverse reaction rates observed in the clinical trials of a drug cannot be directly compared to rates in the clinical trials of another drug and may not reflect the rates observed in practice.

The safety of darifenacin was evaluated in controlled clinical trials in a total of 8,830 patients, 6,001 of whom were treated with darifenacin. Of this total, 1,069 patients participated in three, 12-week, randomized, placebo-controlled, fixed-dose efficacy and safety studies (Studies 1, 2 and 3). Of this total, 337 and 334 patients received darifenacin 7.5 mg daily and 15 mg daily, respectively. In all long-term trials combined, 1,216 and 672 patients received treatment with darifenacin for at least 24 and 52 weeks, respectively.

In Studies 1, 2 and 3 combined, the serious adverse reactions to darifenacin were urinary retention and constipation.

In Studies 1, 2 and 3 combined, dry mouth leading to study discontinuation occurred in 0 %, 0.9 %, and 0 % of patients treated with darifenacin 7.5 mg daily, darifenacin 15 mg daily and placebo, respectively. Constipation leading to study discontinuation occurred in 0.6 %, 1.2 %, and 0.3 % of patients treated with darifenacin 7.5 mg daily, darifenacin 15 mg daily and placebo, respectively.

Table 1 lists the rates of identified adverse reactions, derived from all reported adverse events in 2 % or more of patients treated with 7.5 mg or 15 mg darifenacin, and greater than placebo in Studies 1, 2 and 3. In these studies, the most frequently reported adverse reactions were dry mouth and constipation. The majority of the adverse reactions were mild or moderate in severity and most occurred during the first two weeks of treatment.

Table 1: Incidence of Identified Adverse Reactions, Derived from All Adverse Events Reported in greater than or equal to 2 % of Patients Treated with Darifenacin Extended-Release Tablets and More Frequent with Darifenacin than with Placebo in Studies 1, 2, and 3
Body System | A d v er se Reaction | % age of Subjects
 |  | Darifenacin 7.5 mg N = 337 | Darifenacin 15 mg N = 334 | Placebo N = 388
Digestive | Dry Mouth | 20.2 | 35.3 | 8.2
 | Constipation | 14.8 | 21.3 | 6.2
 | Dyspepsia | 2.7 | 8.4 | 2.6
 | Abdominal Pain | 2.4 | 3.9 | 0.5
 | Nausea | 2.7 | 1.5 | 1.5
 | Diarrhea | 2.1 | 0.9 | 1.8
Urogenital | Urinary Tract Infection | 4.7 | 4.5 | 2.6
Nervous | Dizziness | 0.9 | 2.1 | 1.3
Body as a Whole | Asthenia | 1.5 | 2.7 | 1.3
Eye | Dry Eyes | 1.5 | 2.1 | 0.5

Other adverse reactions reported by 1% to 2% of darifenacin-treated patients include: abnormal vision, accidental injury, back pain, dry skin, flu syndrome, hypertension, vomiting, peripheral edema, weight gain, arthralgia, bronchitis, pharyngitis, rhinitis, sinusitis, rash, pruritus, urinary tract disorder and vaginitis.

Study 4 was a randomized, 12-week, placebo-controlled, dose-titration regimen study in which darifenacin was administered in accordance with dosing recommendations [see Dosage and Administration (2)]. All patients initially received placebo or darifenacin 7.5 mg daily, and after two weeks, patients and physicians were allowed to adjust upward to darifenacin 15 mg if needed. In this study, the most commonly reported adverse reactions were also constipation and dry mouth. Table 2 lists the identified adverse reactions, derived from all adverse events reported in greater than 3% of patients treated with darifenacin and greater than placebo.

Table 2: Number (%) of Adverse Reactions, Derived from All Adverse Events Reported in greater than 3% of Patients Treated with Darifenacin Extended-Release Tablets, and More Frequent with Darifenacin than Placebo, in Study 4
A d v er se Reaction | Darifenacin 7.5 mg/15 mg | Placebo
 | N = 268 | N = 127
Constipation | 56 (20.9 %) | 10 (7.9 %)
Dry Mouth | 50 (18.7 %) | 11 (8.7 %)
Headache | 18 (6.7 %) | 7 (5.5 %)
Dyspepsia | 12 (4.5 %) | 2 (1.6 %)
Nausea | 11 (4.1 %) | 2 (1.6 %)
Urinary Tract Infection | 10 (3.7 %) | 4 (3.1 %)
Accidental Injury | 8 (3.0 %) | 3 (2.4 %)
Flu Syndrome | 8 (3.0 %) | 3 (2.4 %)

6.2 Post Marketing Experience

The following adverse reactions have been reported during post-approval use of darifenacin extended-release tablets. Because these reactions are reported voluntarily from a population of uncertain size, it is not always possible to reliably estimate frequency or establish a causal relationship to drug exposure.

Dermatologic: erythema multiforme, interstitial granuloma annulare

General: hypersensitivity reactions, including angioedema with airway obstruction and anaphylactic reaction

Central Nervous: confusion, hallucinations and somnolence

Cardiovascular: palpitations and syncope

7 DRUG INTERACTIONS

7.1 CYP3A4 Inhibitors

The systemic exposure of darifenacin from darifenacin extended-release tablets is increased in the presence of CYP3A4 inhibitors. The daily dose of darifenacin extended-release tablets should not exceed 7.5 mg when co-administered with potent CYP3A4 inhibitors (for example, ketoconazole, itraconazole, ritonavir, nelfinavir, clarithromycin and nefazadone). No dosing adjustments are recommended in the presence of moderate CYP3A4 inhibitors (for example, erythromycin, fluconazole, diltiazem and verapamil) [see Dosage and Administration (2) and Clinical Pharmacology (12.3)].

7.2 CYP2D6 Inhibitors

No dosing adjustments are recommended in the presence of CYP2D6 inhibitors (for example, paroxetine, fluoxetine, quinidine and duloxetine) [see Clinical Pharmacology (12.3)].

7.3 CYP2D6 Substrates

Caution should be taken when darifenacin extended-release tablets are used concomitantly with medications that are predominantly metabolized by CYP2D6 and which have a narrow therapeutic window (for example, flecainide, thioridazine and tricyclic antidepressants) [see Clinical Pharmacology (12.3)].

7.4 CYP3A4 Substrates

Darifenacin (30 mg daily) did not have a significant impact on midazolam (7.5 mg) pharmacokinetics [see Clinical Pharmacology (12.3)].

7.5 Combination oral contraceptives

Darifenacin (10 mg three times daily) had no effect on the pharmacokinetics of the combination oral contraceptives containing levonorgestrel and ethinyl estradiol [see Clinical Pharmacology (12.3)].

7.6 Warfarin

Darifenacin had no significant effect on prothrombin time when a single dose of warfarin 30 mg was co-administered with darifenacin (30 mg daily) at steady-state. Standard therapeutic prothrombin time monitoring for warfarin should be continued.

7.7 Digoxin

Darifenacin (30 mg daily) did not have a clinically relevant effect on the pharmacokinetics of digoxin (0.25 mg) at steady-state. Routine therapeutic drug monitoring for digoxin should be continued [see Clinical Pharmacology (12.3)].

7.8 Other Anticholinergic Agents

The concomitant use of darifenacin extended-release tablets with other anticholinergic agents may increase the frequency and/or severity of dry mouth, constipation, blurred vision and other anticholinergic pharmacological effects. Anticholinergic agents may potentially alter the absorption of some concomitantly administered drugs due to effects on gastrointestinal motility.

8 USE IN SPECIFIC POPULATIONS

8.1 Pregnancy

Risk Summary

There are no available data on darifenacin use in pregnant women to evaluate for a drug-associated risk of major birth defects, miscarriage, or other adverse maternal or fetal outcomes. In animal studies, darifenacin was not teratogenic in rats and rabbits at plasma exposures of free drug (via AUC) up to 59 and 28 times the maximum recommended human dose (MRHD) of 15 mg, respectively. Effects on embryofetal development were observed following administration of darifenacin during pregnancy (dilated ureter and/or kidney pelvis in rabbits at about 9 times the MRHD, post-implantation loss in rabbits at about 28 times, and delayed ossification in rats at about 59 times) and during pregnancy and lactation (developmental delays in rats at about 17 times the MRHD), which was associated with maternal toxicity (see Data). Dystocia was observed in rat dams at about 17 times the MRHD.

In the U.S. general population, the estimated background risk of major birth defects and miscarriage in clinically recognized pregnancies is 2 to 4% and 15 to 20%, respectively.

Data

Animal Data

Embryofetal development studies were conducted with oral darifenacin in female rats (0, 3, 10, and 50 mg/kg/day) and rabbits (0, 3, 10, and 30 mg/kg/day) during the period of organogenesis (gestation days 6 to 17 in the rat and gestation days 6 to 18 in the rabbit). Darifenacin was not teratogenic in rats and rabbits at plasma exposure of free drug (via AUC) up to 59 times and 28 times, respectively (doses up to 50 and 30 mg/kg/day, respectively) the maximum recommended human dose [MRHD] of 15 mg.

At approximately 59 times the MRHD in pregnant rats there was a delay in the ossification of the sacral and caudal vertebrae (associated with a decrease in maternal and pup body weight gains) which was not observed at an exposure approximately 13 times the AUC at the MRHD. At five times the AUC (3 mg/kg/day), there were no effects on dams or pups.

In pregnant rabbits, an exposure of darifenacin approximately 28 times the AUC at the MRHD of 15mg (30 mg/kg/day) was shown to increase post-implantation loss (associated with decreased maternal body weight gain), with a no effect level at 10 mg/kg/day (9 times the AUC at the MRHD). Dilated ureter and/or kidney pelvis was also observed in offspring at this highest dose along with urinary bladder dilation consistent with the pharmacological action of darifenacin, with one case observed at the mid dose of 10 mg/kg/day (9 times the MRHD). No effect was observed at the lowest dose of 3 mg/kg/day (approximately 2.8 times the AUC at the MRHD).

A pre- and post-natal development study was conducted with oral darifenacin in female rats (0, 3, 10, and 50 mg/kg/day) throughout gestation and lactation. Decreased body weight gain and dystocia were observed in dams at 10 mg/kg/day) throughout gestation and lactation. Decreased body weight and dystocia were observed in dams at 10 mg/kg/day (approximately 17 times the MRHD) and above. Slight developmental delays (surface righting reflex, incisor eruption, eyelid opening, vaginal opening, preputial separation) were observed in pups at these doses. At 5 times the AUC at the MRHD (3 mg/kg/day), there were no effects on dams or pups.

8.2 Lactation

Risk Summary

There are no data on the presence of darifenacin in human milk, the effects on the breastfed infant, or the effects of darifenacin on milk production. Darifenacin is present in rat milk [see Data]. When a drug is present in animal milk, it is likely that the drug will be present in human milk.

The developmental and health benefits of breastfeeding should be considered along with the mother's clinical need for darifenacin and any potential adverse effects on the breastfed child from darifenacin or from the underlying maternal conditions.

Data

After a single oral dose of ^14C radiolabeled darifenacin to lactating rats, darifenacin was detected in maternal milk.

8.4 Pediatric Use

The safety and effectiveness of darifenacin extended-release tablets in pediatric patients have not been established.

8.5 Geriatric Use

In the fixed-dose, placebo-controlled, clinical studies, 30% of patients treated with darifenacin were over 65 years of age. No overall differences in safety or efficacy were observed between patients over 65 years (n = 207) and younger patients less than 65 years (n = 464). No dose adjustment is recommended for elderly patients [see Clinical Pharmacology (12.3) and Clinical Studies (14)] .

8.6 Hepatic Impairment

Subjects with severe hepatic impairment (Child-Pugh C) have not been studied, therefore darifenacin extended-release tablets are not recommended for use in these patients [see Dosage and Administration (2) and Warnings and Precautions (5.6)] . The daily dose of darifenacin extended-release tablets should not exceed 7.5 mg once daily for patients with moderate hepatic impairment (Child-Pugh B) [see Dosage and Administration (2) and Warnings and Precautions (5.6)] . After adjusting for plasma protein binding, unbound darifenacin exposure was estimated to be 4.7-fold higher in subjects with moderate hepatic impairment than subjects with normal hepatic function. No dose adjustment is recommended for patients with mild hepatic impairment (Child-Pugh A).

8.7 Renal Impairment

A study of subjects with varying degrees of renal impairment (creatinine clearance between 10 and 136 mL/min) demonstrated no clear relationship between renal function and darifenacin clearance. No dose adjustment is recommended for patients with renal impairment [see Clinical Pharmacology (12.3)] .

8.8 Gender

No dose adjustment is recommended based on gender [see Clinical Pharmacology (12.3) and Clinical Studies(14)] .

10 OVERDOSAGE

Overdosage with antimuscarinic agents, including darifenacin extended-release tablets, can result in severe antimuscarinic effects. Treatment should be symptomatic and supportive. In the event of overdosage, ECG monitoring is recommended. Darifenacin extended-release tablets has been administered in clinical trials at doses up to 75 mg (five times the maximum therapeutic dose) and signs of overdose were limited to abnormal vision.

11 DESCRIPTION

Darifenacin extended-release tablet is an extended-release tablet for oral administration which contains 7.5 mg or 15 mg darifenacin as its hydrobromide salt. The active moiety, darifenacin, is a potent muscarinic receptor antagonist.

Chemically, darifenacin hydrobromide is (S)-2-{1-[2-(2,3-dihydrobenzofuran-5-yl)ethyl]-3-pyrrolidinyl}-2,2-diphenylacetamide hydrobromide. The empirical formula of darifenacin hydrobromide is C 28H 30N 2O 2•HBr.

The structural formula is:

Darifenacin hydrobromide is a white to almost white to off-white powder, with a molecular weight of 507.5.

Darifenacin extended-release tablet is a once-a-day extended-release tablet and contains the following inactive ingredients: colloidal silicon dioxide, hypromellose (E15 LV), hypromellose (methocel K4M CR), magnesium stearate, microcrystalline cellulose, polyethylene glycol 400, talc and titanium dioxide. The 15 mg tablet also contains ferric oxide red and ferric oxide yellow.

12 CLINICAL PHARMACOLOGY

12.1 Mechanism of Action

Darifenacin is a competitive muscarinic receptor antagonist. Muscarinic receptors play a role in cholinergically mediated functions, including contractions of the urinary bladder smooth muscle.

In vitro studies using human recombinant muscarinic receptor subtypes show that darifenacin has greater affinity for the M 3 receptor than for the other known muscarinic receptors (9- and 12-fold greater affinity for M 3 compared to M 1 and M 5, respectively, and 59-fold greater affinity for M 3 compared to both M 2 and M 4). M 3 receptors are involved in contraction of human bladder.

12.2 Pharmacodynamics

In three cystometric studies performed in patients with involuntary detrusor contractions, increased bladder capacity was demonstrated by an increased volume threshold for unstable contractions and diminished frequency of unstable detrusor contractions after darifenacin extended-release tablet treatment. These findings are consistent with an antimuscarinic action on the urinary bladder.

Electrophysiology

The effect of a six-day treatment of 15 mg and 75 mg darifenacin on QT/QTc interval was evaluated in a multiple-dose, double-blind, randomized, placebo- and active-controlled (moxifloxacin 400 mg) parallel-arm design study in 179 healthy adults (44% male, 56% female) aged 18 to 65. Subjects included 18% poor metabolizers (PMs) and 82% extensive metabolizers (EMs). The QT interval was measured over a 24-hour period both predosing and at steady-state. The 75 mg darifenacin extended-release tablets dose was chosen because this achieves exposure similar to that observed in CYP2D6 poor metabolizers administered the highest recommended dose (15 mg) of darifenacin in the presence of a potent CYP3A4 inhibitor. At the doses studied, darifenacin did not result in QT/QTc interval prolongation at any time during the steady-state, while moxifloxacin treatment resulted in a mean increase from baseline QTcF of about 7.0 msec when compared to placebo. In this study, darifenacin 15 mg and 75 mg doses demonstrated a mean heart rate change of 3.1 and 1.3 bpm, respectively, when compared to placebo. However, in the clinical efficacy and safety studies, the change in median HR following treatment with darifenacin was no different from placebo.

12.3 Pharmacokinetics

Absorption

After oral administration of darifenacin extended-release tablets to healthy volunteers, peak plasma concentrations of darifenacin are reached approximately seven hours after multiple dosing and steady-state plasma concentrations are achieved by the sixth day of dosing. The mean (SD) steady-state time course of darifenacin 7.5 mg and 15 mg extended-release tablets is depicted in Figure 1.

Figure 1 Mean (SD) Steady-State Darifenacin Plasma Concentration-Time Profiles for Darifenacin 7.5 mg and 15 mg in Healthy Volunteers Including Both CYP2D6 EMs and PMs*

*Includes 95 EMs and 6 PMs for 7.5 mg; 104 EMs and 10 PMs for 15 mg.

A summary of mean (standard deviation, SD) steady-state pharmacokinetic parameters of darifenacin 7.5 mg and 15 mg extended-release tablets in EMs and PMs of CYP2D6 is provided in Table 3.

Table 3: Mean (SD) Steady-State Pharmacokinetic Parameters from Darifenacin 7.5 mg and 15 mg Extended-Release Tablets Based on Pooled Data by Predicted CYP2D6 Phenotype
 | Darifenacin 7.5 mg (N = 68 EM, 5 PM) |  |  |  |  | Darifenacin 15 mg (N = 102 EM, 17 PM)
 | A UC 24 (ng•h/mL) | Cmax (ng/mL) | Cavg (ng/mL) | Tmax (h) | t 1/2 (h) | A UC 24 (ng•h/mL) | Cmax (ng/mL) | Cavg (ng/mL) | Tmax (h) | t 1/2 (h)
EM | 29.24 | 2.01 | 1.22 | 6.49 | 12.43 | 88.90 | 5.76 | 3.70 | 7.61 | 12.05
 | (15.47) | (1.04) | (0.64) | (4.19) | (5.64) a | (67.87) | (4.24) | (2.83) | (5.06) | (12.37) b
PM | 67.56 | 4.27 | 2.81 | 5.20 | 19.95 c | 157.71 | 9.99 | 6.58 | 6.71 | 7.40 d
 | (13.13) | (0.98) | (0.55) | (1.79) | - | (77.08) | (5.09) | (3.22) | (3.58) | -
aN = 25; bN = 8; cN = 2; dN = 1; AUC 24 = Area under the plasma concentration versus time curve for 24h;
C max = Maximum observed plasma concentration; C avg = Average plasma concentration at steady-state;
T max = Time of occurrence of Cmax; t 1/2 = Terminal elimination half-life. Regarding EM and PM [see Clincal Pharmacology, Pharmacokinetics, Variability in Metabolism (12.3)].

The mean oral bioavailability of darifenacin extended-release tablets in EMs at steady-state is estimated to be 15% and 19% for 7.5 mg and 15 mg tablets, respectively.

Effect of Food

Following single dose administration of darifenacin extended-release tablets with food, the AUC of darifenacin was not affected, while the C max was increased by 22% and T max was shortened by 3.3 hours. There is no effect of food on multiple-dose pharmacokinetics from darifenacin extended-release tablets.

Distribution

Darifenacin is approximately 98 % bound to plasma proteins (primarily to alpha-1-acid-glycoprotein). The steady-state volume of distribution (Vss) is estimated to be 163 L.

Metabolism

Darifenacin is extensively metabolized by the liver following oral dosing.

Metabolism is mediated by cytochrome P450 enzymes CYP2D6 and CYP3A4. The three main metabolic routes are as follows:

(i) monohydroxylation in the dihydrobenzofuran ring;

(ii) dihydrobenzofuran ring opening;

(iii) N-dealkylation of the pyrrolidine nitrogen.

The initial products of the hydroxylation and N-dealkylation pathways are the major circulating metabolites but they are unlikely to contribute significantly to the overall clinical effect of darifenacin.

Variability in Metabolism

A subset of individuals (approximately 7% Caucasians and 2% African Americans) are poor metabolizers (PMs) of CYP2D6 metabolized drugs. Individuals with normal CYP2D6 activity are referred to as extensive metabolizers (EMs). The metabolism of darifenacin in PMs will be principally mediated via CYP3A4. The darifenacin ratios (PM versus EM) for C max and AUC following darifenacin 15 mg once daily at steady-state were 1.9 and 1.7, respectively.

Excretion

Following administration of an oral dose of ^14C-darifenacin solution to healthy volunteers, approximately 60% of the radioactivity was recovered in the urine and 40% in the feces. Only a small percentage of the excreted dose was unchanged darifenacin (3%). Estimated darifenacin clearance is 40 L/h for EMs and 32 L/h for PMs. The elimination half-life of darifenacin following chronic dosing is approximately 13 to 19 hours.

Drug-Drug Interactions

Effects of Other Drugs on Darifenacin

Darifenacin metabolism is primarily mediated by the cytochrome P450 enzymes CYP2D6 and CYP3A4. Therefore, inducers of CYP3A4 or inhibitors of either of these enzymes may alter darifenacin pharmacokinetics [see Drug Interactions (7)] .

CYP3A4 Inhibitors: In a drug interaction study, when a 7.5 mg once daily dose of darifenacin was given to steady- state and co-administered with the potent CYP3A4 inhibitor ketoconazole 400 mg, mean darifenacin Cmax increased to 11.2 ng/mL for EMs (n = 10) and 55.4 ng/mL for one PM subject (n = 1). Mean AUC increased to 143 and 939 ng •h/mL for EMs and for one PM subject, respectively. When a 15 mg daily dose of darifenacin was given with ketoconazole, mean darifenacin Cmax increased to 67.6 ng/mL and 58.9 ng/mL for EMs (n = 3) and one PM subject (n = 1), respectively. Mean AUC increased to 1,110 and 931 ng •h/mL for EMs and for one PM subject, respectively [see Dosage and Administration (2) and Drug Interactions (7.1)] .

The mean C max and AUC of darifenacin following 30 mg once daily dosing at steady-state were 128% and 95% higher, respectively, in the presence of a moderate CYP3A4 inhibitor, erythromycin. Co-administration of fluconazole, a moderate CYP3A4 inhibitor and darifenacin 30 mg once daily at steady-state increased darifenacin C max and AUC by 88 % and 84 %, respectively [see Drug Interactions (7.1)] .

The mean C max and AUC of darifenacin following 30 mg once daily at steady-state were 42 % and 34 % higher, respectively, in the presence of cimetidine, a mixed CYP P450 enzyme inhibitor.

CYP2D6 Inhibitors: Darifenacin exposure following 30 mg once daily at steady-state was 33 % higher in the presence of the potent CYP2D6 inhibitor paroxetine 20 mg [see Drug Interactions (7.2)] .

Effects of Darifenacin on Other Drugs

In Vitro Studies: Based on in vitro human microsomal studies, darifenacin extended-release tablets are not expected to inhibit CYP1A2 or CYP2C9 at clinically relevant concentrations.

In Vivo Studies: The potential for clinical doses of darifenacin extended-release tablets to act as inhibitors of CYP2D6 or CYP3A4 substrates was investigated in specific drug interaction studies.

CYP2D6 Substrates: The mean C max and AUC of imipramine, a CYP2D6 substrate, were increased by 57% and 70%, respectively, in the presence of steady-state darifenacin 30 mg once daily. The mean C max and AUC of desipramine, the active metabolite of imipramine, were increased by 260 % [see Drug Interactions (7.3)] .

CYP3A4 Substrates: Darifenacin (30 mg daily) co-administered with a single oral dose of midazolam 7.5 mg resulted in a 17 % increase in midazolam exposure.

Combination Oral Contraceptives: Darifenacin (10 mg three times daily) had no effect on the pharmacokinetics of a combination oral contraceptive containing levonorgestrel (0.15 mg) and ethinyl estradiol (0.03 mg).

Warfarin: Darifenacin had no significant effect on prothrombin time when a single dose of warfarin 30 mg was co-administered with darifenacin (30 mg daily) at steady-state [see Drug Interactions (7.6)] .

Digoxin: Darifenacin (30 mg daily) co-administered with digoxin (0.25 mg) at steady-state resulted in a 16 % increase in digoxin exposure [see Drug Interactions (7.7)] .

Pharmacokinetics in Special Populations

Age: A population pharmacokinetic analysis of patient data indicated a trend for clearance of darifenacin to decrease with age (6% per decade relative to a median age of 44). Following administration of darifenacin 15 mg once daily, darifenacin exposure at steady-state was approximately 12% to 19% higher in volunteers between 45 and 65 years of age compared to younger volunteers aged 18 to 44 years [see Use in Specific Populations (8.5)].

Pediatric: The pharmacokinetics of darifenacin extended-release tablets has not been studied in the pediatric population [see Use in Specific Populations (8.4)] .

Gender: PK parameters were calculated for 22 male and 25 female healthy volunteers. Darifenacin Cmax and AUC at steady-state were approximately 57% to 79% and 61% to 73% higher in females than in males, respectively [see Use in Specific Populations (8.8)] .

Renal Impairment: A study of subjects with varying degrees of renal impairment (creatinine clearance between 10 and 136 mL/min) given darifenacin 15 mg once daily to steady-state demonstrated no clear relationship between renal function and darifenacin clearance [see Use in Specific Populations (8.7)] .

Hepatic Impairment: Darifenacin pharmacokinetics were investigated in subjects with mild (Child-Pugh A) or moderate (Child-Pugh B) impairment of hepatic function given darifenacin 15 mg once daily to steady-state. Mild hepatic impairment had no effect on the pharmacokinetics of darifenacin. However, protein binding of darifenacin was affected by moderate hepatic impairment. After adjusting for plasma protein binding, unbound darifenacin exposure was estimated to be 4.7-fold higher in subjects with moderate hepatic impairment than subjects with normal hepatic function. Subjects with severe hepatic impairment (Child-Pugh C) have not been studied [see Dosage and Administration (2), Warning and Precautions (5.5) and Use in Specific Population (8.6)] .

13 NONCLINICAL TOXICOLOGY

13.1 Carcinogenesis, Mutagenesis, Impairment of Fertility

Carcinogenesis

Carcinogenicity studies with darifenacin were conducted in mice and rats. No evidence of drug-related carcinogenicity was revealed in a 24-month study in mice at dietary doses up to 100 mg/kg/day or approximately 32 times the estimated free plasma AUC reached at the maximum recommended human dose (the AUC at the MRHD) of 15 mg and in a 24-month study in rats at doses up to 15 mg/kg/day or up to approximately 12 times the AUC at the MRHD in female rats and approximately eight times the AUC at the MRHD in male rats.

Mutagenesis

Darifenacin was not genotoxic in the bacterial mutation assay (Ames test), the Chinese hamster ovary assay, the human lymphocyte assay, or the in vivo mouse bone marrow cytogenetics assay.

Impairment of Fertility

There was no evidence for effects on fertility in male or female rats treated at oral doses associated with up to approximately 78 times (50 mg/kg/day) the AUC at the MRHD.

14 CLINICAL STUDIES

Darifenacin extended-release tablets were evaluated for the treatment of patients with overactive bladder with symptoms of urgency, urge urinary incontinence, and increased urinary frequency in three randomized, fixed-dose, placebo-controlled, multicenter, double-blind, 12-week studies (Studies 1, 2 and 3) and one randomized, double-blind, placebo-controlled, multicenter, dose-titration study (Study 4). For study eligibility in all four studies, patients with symptoms of overactive bladder for at least six months were required to demonstrate at least eight micturitions and at least one episode of urinary urgency per day, and at least five episodes of urge urinary incontinence per week. The majority of patients were white (94%) and female (84%), with a mean age of 58 years, range 19 to 93 years. Thirty-three percent of patients were greater than or equal to 65 years of age . These characteristics were well balanced across treatment groups. The study population was inclusive of both naïve patients who had not received prior pharmacotherapy for overactive bladder (60%) and those who had (40%).

Table 4 shows the efficacy data collected from 7- or 14-day voiding diaries in the three fixed-dose placebo-controlled studies of 1,059 patients treated with placebo, 7.5 mg or 15 mg once daily darifenacin for 12 weeks. A significant decrease in the primary endpoint, change from baseline in average weekly urge urinary incontinence episodes was observed in all three studies. Data is also shown for two secondary endpoints, change from baseline in the average number of micturitions per day (urinary frequency) and change from baseline in the average volume voided per micturition.

Table 4: Difference Between Darifenacin (7.5 mg, 15 mg) and Placebo for the Week 12 Change from Baseline (Studies 1, 2 and 3)
 | Study 1 |  |  | Study 2 |  |  | Study 3
 | Darifenacin 7.5 mg | Darifenacin 15 mg | Placebo | Darifenacin 7.5 mg | Darifenacin 15 mg | Placebo | Darifenacin 15 mg | Placebo
No. of Patients Entered | 229 | 115 | 164 | 108 | 107 | 109 | 112 | 115
Urge Incontinence Episodes per Week
Median Baseline | 16.3 | 17.0 | 16.6 | 14.0 | 17.3 | 16.1 | 16.2 | 15.5
Median Change from Baseline | -9.0 | -10.4 | -7.6 | -8.1 | -10.4 | -5.9 | -11.4 | -9.0
Median Difference to Placebo | -1.5* | -2.1* | - | -2.8* | -4.3* | - | -2.4* | -
Micturitions per Day
Median Baseline | 10.1 | 10.1 | 10.1 | 10.3 | 11.0 | 10.1 | 10.5 | 10.4
Median Change from Baseline | -1.6 | -1.7 | -0.8 | -1.7 | -1.9 | -1.1 | -1.9 | -1.2
Median Difference to Placebo | -0.8* | -0.9* | - | -0.5 | -0.7* | - | -0.5 | -
Volume of Urine Passed per Void (mL)
Median Baseline | 160.2 | 151.8 | 162.4 | 161.7 | 157.3 | 162.2 | 155.0 | 147.1
Median Change from Baseline | 14.9 | 30.9 | 7.6 | 16.8 | 23.6 | 7.1 | 26.7 | 4.6
Median Difference to Placebo | 9.1* | 20.7* | - | 9.2 | 16.6* | - | 20.1* | -
*Indicates statistically significant difference versus placebo (p less than 0.05, Wilcoxon rank-sum test)

Table 5 shows the efficacy data from the dose-titration study in 395 patients who initially received 7.5 mg darifenacin or placebo daily with the option to increase to 15 mg darifenacin or placebo daily after two weeks.

Table 5: Difference between Darifenacin (7.5 mg/15 mg) and Placebo for the Week 12 Change from Baseline (Study 4)
 | Darifenacin 7.5 mg /15 mg | Placebo
No. of Patients Treated | 268 | 127
Urge Incontinence Episodes per Week
Median Baseline Median Change from Baseline Median Difference to Placebo | 16.0 -8.2 -1.4* | 14.0 -6.0 -
Micturitions per Day
Median Baseline Median Change from Baseline Median Difference to Placebo | 9.9 -1.9 -0.8* | 10.4 -1.0 -
Volume of Urine Passed per Void (mL)
Median Baseline | 173.7 | 177.2
Median Change from Baseline Median Difference to Placebo | 18.8 13.3 * | 6.6 -
*Indicates statistically significant difference versus placebo (p less than 0.05, Wilcoxon rank-sum test)

As seen in Figures 2a, 2b and 2c, reductions in the number of urge incontinence episodes per week were observed within the first two weeks in patients treated with darifenacin 7.5 mg and 15 mg once daily compared to placebo. Further, these effects were sustained throughout the 12-week treatment period.

Figures 2a, 2b, 2c. Median Change from Baseline at Weeks 2, 6, 12 for Number of Urge Incontinence Episodes per Week (Studies 1, 2 and 3)

Figure 2a, Study 1

Figure 2b, Study 2

Figure 2c, Study 3

16 HOW SUPPLIED/STORAGE AND HANDLING

Darifenacin extended-release tablets, 7.5 mg are white to off-white colored, round, biconvex, bevel edged, film coated tablets, debossed "202" on one side and plain on other side.

Bottle of 30.............................................................................................NDC 13668-202-30

Bottle of 90.............................................................................................NDC 13668-202-90

Bottle of 500..........................................................................................NDC 13668-202-05

Darifenacin extended-release tablets, 15 mg are light peach colored, round, biconvex, bevel edged, film coated tablets, debossed "203" on one side and plain on other side.

Bottle of 30........................................................................................... NDC 13668-203-30

Bottle of 90........................................................................................... NDC 13668-203-90

Bottle of 500..........................................................................................NDC 13668-203-05

Storage

Store at 20° to 25°C (68° to 77°F); excursions permitted between 15°C and 30°C (59°F and 86°F) [see USP Controlled Room Temperature]. Protect from light.

Keep this and all drugs out of the reach of children.

17 PATIENT COUNSELING INFORMATION

8100851See FDA-approved patient labeling (Patient Information).

Patients should be informed that anticholinergic agents, such as darifenacin extended-release tablets, may produce clinically significant adverse effects related to anticholinergic pharmacological activity including constipation, urinary retention and blurred vision. Heat prostration (due to decreased sweating) can occur when anticholinergics such as darifenacin extended-release tablets are used in a hot environment. Because anticholinergics, such as darifenacin extended-release tablets, may produce dizziness or blurred vision, patients should be advised to exercise caution in decisions to engage in potentially dangerous activities until the drug's effects have been determined. Patients should read the patient information leaflet before starting therapy with darifenacin extended-release tablets.

Patients should be informed that darifenacin may produce clinically significant angioedema that may result in airway obstruction. Patients should be advised to promptly discontinue darifenacin therapy and seek immediate medical attention if they experience edema of the tongue or laryngopharynx, or difficulty breathing.

Darifenacin extended-release tablets should be taken once daily with water. They may be taken with or without food, and should be swallowed whole and not chewed, divided or crushed.

Manufactured by:

TORRENT PHARMACEUTICALS LTD., INDIA.

Manufactured for:

TORRENT PHARMA INC., Basking Ridge, NJ 07920

8106506 Revised: January 2026

FDA-Approved Patient Labeling

Darifenacin (DAR-i-FEN-a-sin)Extended-Release Tablets

Read this Patient Information leaflet about darifenacin extended-release tablets before you start taking it and each time you get a refill. There may be new information. This leaflet does not take the place of talking to your doctor about your medical condition or your treatment.

What is darifenacin extended-release tablets?

Darifenacin extended-release tablets is a prescription medicine for adults used to treat the following symptoms due to a condition called overactive bladder:

- Urge urinary incontinence: a strong need to urinate with leaking or wetting accidents
- Urgency: a strong need to urinate right away
- Frequency: urinating often

It is unknown if darifenacin extended-release tablets is safe and effective in children.

Who should not take darifenacin extended-release tablets?

Do not take darifenacin extended-release tablets if you:

- are not able to empty your bladder ("urinary retention")
- have delayed or slow emptying of your stomach ("gastric retention")
- have an eye problem called "uncontrolled narrow-angle glaucoma"

What should I tell my healthcare provider before starting darifenacin extended-release tablets?

Before starting darifenacin extended-release tablets, tell your doctor if you:

- have trouble emptying your bladder or if you have a weak urine stream
- have any stomach or intestinal problems, or problems with constipation
- have liver problems
- have any other medical conditions
- are pregnant or are planning to become pregnant. It is not known if darifenacin extended-release tablets can harm your unborn baby.
- are breastfeeding or plan to breastfeed. It is not known if darifenacin passes into breast milk and if it can harm your baby. Talk to your doctor about the best way to feed your baby if you take darifenacin extended-release tablets.

Tell your healthcare provider about all the medicines you take, including prescription and non-prescription medicines, vitamins, and herbal supplements. Darifenacin extended-release tablets and certain other medicines may affect each other, causing side effects.

Especially tell your healthcare provider if you take a:

- antifungal medicine ketoconazole (Nizoral®) or itraconazole (Sporanox®)
- antibiotic medicine clarithromycin (Biaxin®)
- anti-HIV medicine ritonavir (Norvir®) or nelfinavir (Viracept®)
- medicine to treat depression nefazadone (Serzone®)
- medicine to treat an abnormal heartbeat flecainide (TambocorTM)
- antipsychotic medicine thioridazine (Mellaril®)
- medicine to treat depression called a tricyclic antidepressant

Know all the medicines you take. Keep a list of them with you to show your doctor and pharmacist each time you get a new medicine.

How should I take darifenacin extended-release tablets?

- Take darifenacin extended-release tablets exactly as prescribed. Your doctor will prescribe the dose that is right for you. Take darifenacin extended-release tablets 1 time daily with water.
- Darifenacin extended-release tablets should be swallowed whole. Do not chew, cut or crush darifenacin extended-release tablets.
- Darifenacin extended-release tablets may be taken with or without food.
- If you take too much darifenacin extended-release tablets call your doctor or go to the nearest hospital emergency room right away.

What should I avoid while taking darifenacin extended-release tablets?

Darifenacin extended-release tablets can cause blurred vision or dizziness. Do not drive or operate heavy machinery until you know how darifenacin extended-release tablets affects you.

What are the possible side effects of darifenacin extended-release tablets?

Darifenacin extended-release tablets may cause serious side effects including:

- Serious allergic reaction. Stop taking darifenacin extended-release tablets and get medical help right away if you have:
- hives, skin rash or swelling
- severe itching
- swelling of your face, mouth or tongue
- trouble breathing

The most common side effects with darifenacin extended-release tablets are:

- constipation
- dry mouth
- headache
- heartburn
- nausea
- urinary tract infection
- blurred vision
- heat exhaustion or heat-stroke. This can happen when darifenacin extended-release tablets are used in hot environments. Symptoms of heat exhaustion may include:
- decreased sweating
- dizziness
- tiredness
- nausea
- increase body temperature

Tell your doctor if you have any side effect that bothers you or that does not go away.

These are not all the possible side effects of darifenacin extended-release tablets. For more information, ask your doctor or pharmacist.

Call your doctor for medical advice about side effects. You may report side effects to FDA at 1-800-FDA-1088.

How do I store darifenacin extended-release tablets?

Store darifenacin extended-release tablets at 20° to 25°C (68° to 77°F); excursions permitted between 15°C and 30°C (59°F and 86°F) [see USP Controlled Room Temperature]. Protect from light.

Keep darifenacin extended-release tablets and all medicines out of the reach of children.

General information about darifenacin extended-release tablets.

Medicines are sometimes prescribed for purposes other than those listed in a Patient Information leaflet. Do not use darifenacin extended-release tablets for a condition for which it was not prescribed. Do not give darifenacin extended-release tablets to other people, even if they have the same symptoms you have. It may harm them.

This Patient Information leaflet summarizes the most important information about darifenacin extended-release tablets. If you would like more information, talk with your doctor. You can ask your pharmacist or doctor for information about darifenacin extended-release tablets that is written for health professionals.

What are the ingredients in darifenacin extended-release tablets?

Active ingredient: darifenacin

Inactive ingredients: colloidal silicon dioxide, hypromellose (E15 LV), hypromellose (methocel K4M CR), magnesium stearate, microcrystalline cellulose, polyethylene glycol 400, talc and titanium dioxide.

The 15 mg tablet also contains ferric oxide red and ferric oxide yellow.

The brands listed are the trademarks of their respective owners.

This Patient Information has been approved by the U.S. Food and Drug Administration.

Manufactured by:

TORRENT PHARMACEUTICALS LTD., INDIA.

Manufactured for:

TORRENT PHARMA INC., Basking Ridge, NJ 07920

8106505 Revised: January 2026

PACKAGE LABEL.PRINCIPAL DISPLAY PANEL

Darifenacin Extended-Release Tablets 7.5 mg: Bottle of 30 Tablets

Darifenacin Extended-Release Tablets 15 mg: Bottle of 30 Tablets